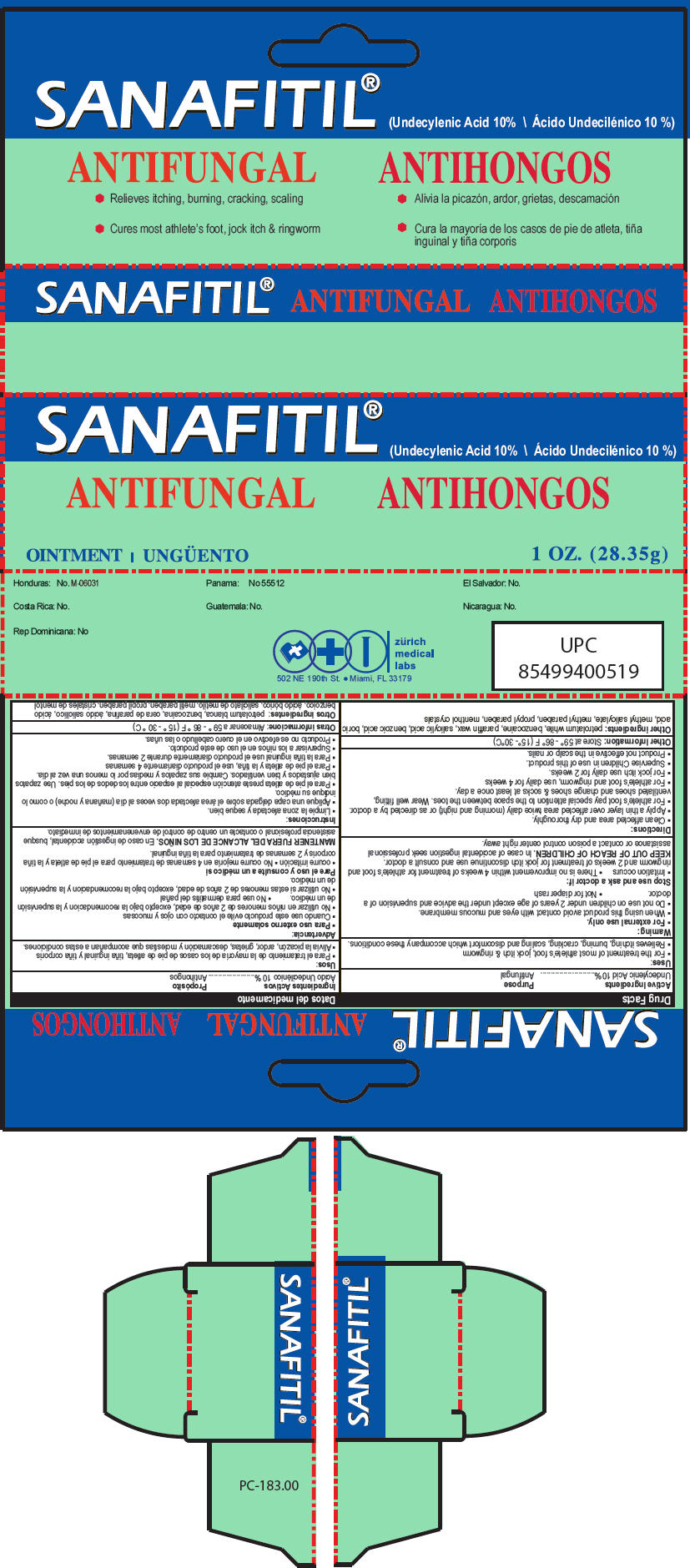 DRUG LABEL: Sanafitil
NDC: 61357-149 | Form: OINTMENT
Manufacturer: ZURICH MEDICAL LABS, LLC
Category: otc | Type: HUMAN OTC DRUG LABEL
Date: 20140321

ACTIVE INGREDIENTS: Undecylenic Acid 100 mg/1 g
INACTIVE INGREDIENTS: PETROLATUM; BENZOCAINE; PARAFFIN; HEXYL SALICYLATE; BENZOIC ACID; BORIC ACID; METHYL SALICYLATE; METHYLPARABEN; PROPYLPARABEN; MENTHOL

Sanafitil® Ungüento

Drug Facts

Active Ingredients

Undecylenic Acid 10%

Purpose

Antifungal

Uses

- For the treatment of most athlete's foot, jock itch & ringworm
- Relieves itching, burning, cracking, scaling and discomfort which accompany these conditions.

Warning

- For external use only.

- When using this product avoid contact with eyes and mucous membrane.

- Do not use on children under 2 years of age except under the advice and supervision of a doctor.
- Not for diaper rash

Stop use and ask a doctor if:

- Irritation occurs
- There is no improvement within 4 weeks of treatment for athlete's foot and ringworm and 2 weeks of treatment for jock itch discontinue use and consult a doctor.

KEEP OUT OF REACH OF CHILDREN. In case of accidental ingestion seek professional assistance or contact a poison control center right away.

Directions

- Clean affected area and dry thoroughly.
- Apply a thin layer over affected area twice daily (morning and night) or as directed by a doctor.
- For athlete's foot pay special attention to the space between the toes. Wear well fitting, ventilated shoes and change shoes & socks at least once a day.
- For athlete's foot and ringworm, use daily for 4 weeks
- For jock itch use daily for 2 weeks.
- Supervise Children in use of this product.
- Product not effective in the scalp or nails.

Other Information

Store at 59° - 86° F (15°- 30°C)

Other ingredients

petrolatum white, benzocaine, paraffin wax, salicylic acid, benzoic acid, boric acid, methyl salicylate, methyl paraben, propyl paraben, menthol crystals

PRINCIPAL DISPLAY PANEL - 28.35 g Tube Carton

SANAFITIL®
(Undecylenic Acid 10%)

ANTIFUNGAL

OINTMENT

1 OZ. (28.35g)